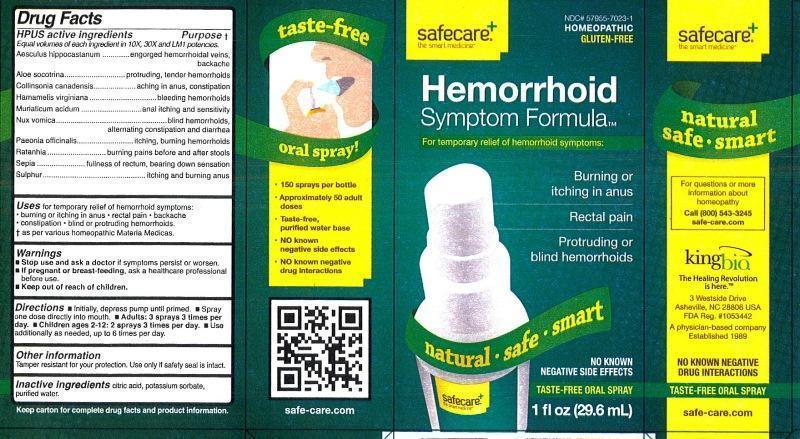 DRUG LABEL: Hemorrhoid Symptom Formula
NDC: 57955-7023 | Form: LIQUID
Manufacturer: King Bio Inc.
Category: homeopathic | Type: HUMAN OTC DRUG LABEL
Date: 20130219

ACTIVE INGREDIENTS: HORSE CHESTNUT 10 [hp_X]/29.6 mL; ALOE 10 [hp_X]/29.6 mL; COLLINSONIA CANADENSIS ROOT 10 [hp_X]/29.6 mL; HAMAMELIS VIRGINIANA ROOT BARK/STEM BARK 10 [hp_X]/29.6 mL; HYDROCHLORIC ACID 10 [hp_X]/29.6 mL; STRYCHNOS NUX-VOMICA SEED 10 [hp_X]/29.6 mL; PAEONIA OFFICINALIS ROOT 10 [hp_X]/29.6 mL; KRAMERIA LAPPACEA ROOT 10 [hp_X]/29.6 mL; SEPIA OFFICINALIS JUICE 10 [hp_X]/29.6 mL; SULFUR 10 [hp_X]/29.6 mL
INACTIVE INGREDIENTS: CITRIC ACID MONOHYDRATE; POTASSIUM SORBATE; WATER

Hemorrhoid Symptom Formula

Active ingredients

HPUS active ingredients

Equal volumes of each ingredient in 10X, 30X, and LM1 potencies.

Aesculus hippocastanum, Aloe socotrina, Collinsonia canadensis, Hamamelis virginiana, Muriaticum acidum, Nux vomica, Paeonia officinalis, Ratanhia, Sepia, Sulphur

Inactive ingredients

Citric acid, potassium sorbate and water

Purpose

HPUS active ingredients Purpose†

Equal volumes of each ingredient in 10X, 30X, and LM1 potencies.

Aesculus hippocastanum.....................................................engorged hemorrhoidal veins, backache

Aloe socotrina.....................................................................protruding, tender hemorrhoids

Collinsonia canadensis.......................................................aching and itching in anus, constipation

Hamamelis virginiana..........................................................bleeding hemorrhoids

Muriaticum acidum..............................................................anal itching and sensitivity

Nux vomica.........................................................................blind hemorrhoids, alternating constipation and diarrhea

Paeonia officinalis...............................................................itching, burning hemorrhoids

Ratanhia.............................................................................burning pains before and after stools

Sepia..................................................................................fullness of rectum, bearing down sensation

Sulphur...............................................................................itching and burning anus

Indications and Usage

Uses for temporary releif of hemorrhold symptoms:

- burning or aching in anus
- rectal pain and itching
- backache
- constipation
- blind or protruding hemorrhoids

† as per various homeopathic Materia Medicas.

Warnings

- Stop use and ask a doctor if symptoms persist or worsen
- If pregnant or breast-feeding, ask a healthcare professional before use.
- Keep out of reach of children.

Other information

Tamper resistant for your protection. Use only if safety seal is intact.

Keep out of reach of children.

Dosage and Administration

Directions:

- initially, depress pump until primed.
- spray one dose directly into mouth
- Adults: 3 sprays 3 times per day
- Children ages 2-12: 2 sprays 3 times per day.
- Use additionally as needed, up to 6 times per day.

PACKAGE LABEL

King Bio Inc.

3 Westside Drive

Asheville, NC 28806

For questions or more information about homeopathy call (800) 543-3245 or safe-care.com